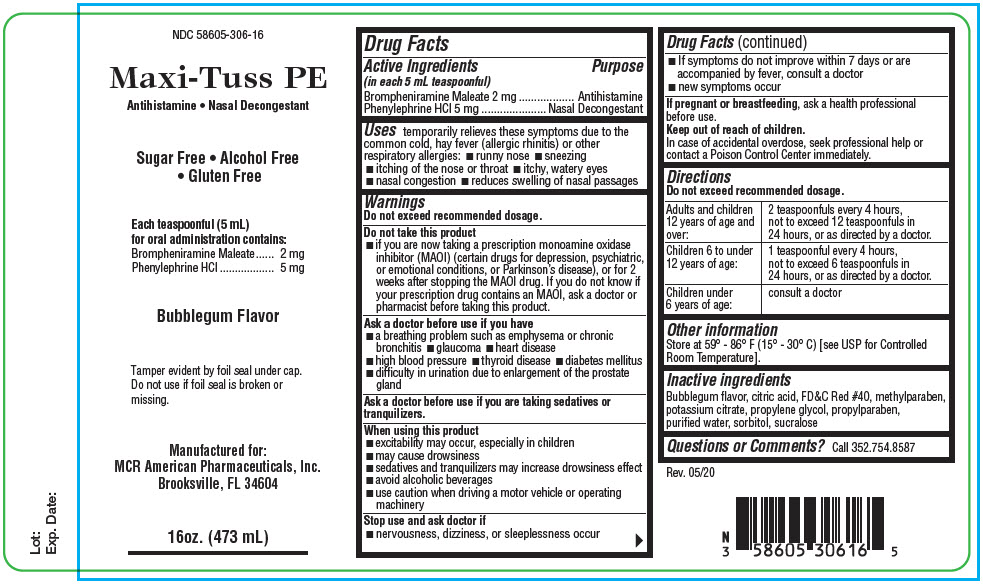 DRUG LABEL: Maxi-Tuss PE
NDC: 58605-306 | Form: LIQUID
Manufacturer: MCR American Pharmaceuticals, Inc.
Category: otc | Type: HUMAN OTC DRUG LABEL
Date: 20200623

ACTIVE INGREDIENTS: BROMPHENIRAMINE MALEATE 2 mg/5 mL; PHENYLEPHRINE HYDROCHLORIDE 5 mg/5 mL
INACTIVE INGREDIENTS: CITRIC ACID MONOHYDRATE; FD&C RED NO. 40; Methylparaben; Potassium Citrate; Propylene Glycol; Propylparaben; WATER; Sorbitol; Sucralose

Maxi-Tuss PE

Drug Facts

ACTIVE INGREDIENT

Active Ingredients (in each 5 mL teaspoonful) | Purpose
Brompheniramine Maleate 2 mg | Antihistamine
Phenylephrine HCl 5 mg | Nasal Decongestant

Uses

temporarily relieves these symptoms due to the common cold, hay fever (allergic rhinitis) or other respiratory allergies:

- runny nose
- sneezing
- itching of the nose or throat
- itchy, watery eyes
- nasal congestion
- reduces swelling of nasal passages

Warnings

Do not exceed recommended dosage.

Do not take this product

- if you are now taking a prescription monoamine oxidase inhibitor (MAOI) (certain drugs for depression, psychiatric, or emotional conditions, or Parkinson's disease), or for 2 weeks after stopping the MAOI drug. If you do not know if your prescription drug contains an MAOI, ask a doctor or pharmacist before taking this product.

Ask a doctor before use if you have

- a breathing problem such as emphysema or chronic bronchitis
- glaucoma
- heart disease
- high blood pressure
- thyroid disease
- diabetes mellitus
- difficulty in urination due to enlargement of the prostate gland

Ask a doctor before use if you are taking sedatives or tranquilizers.

When using this product

- excitability may occur, especially in children
- may cause drowsiness
- sedatives and tranquilizers may increase drowsiness effect
- avoid alcoholic beverages
- use caution when driving a motor vehicle or operating machinery

Stop use and ask doctor if

- nervousness, dizziness, or sleeplessness occur
- If symptoms do not improve within 7 days or are accompanied by fever, consult a doctor
- new symptoms occur

PREGNANCY OR BREAST FEEDING

If pregnant or breastfeeding, ask a health professional before use.

Keep out of reach of children.

In case of accidental overdose, seek professional help or contact a Poison Control Center immediately.

Directions

Do not exceed recommended dosage.

Adults and children 12 years of age and over: | 2 teaspoonfuls every 4 hours, not to exceed 12 teaspoonfuls in 24 hours, or as directed by a doctor.
Children 6 to under 12 years of age: | 1 teaspoonful every 4 hours, not to exceed 6 teaspoonfuls in 24 hours, or as directed by a doctor.
Children under 6 years of age: | consult a doctor

Other information

Store at 59° - 86° F (15° - 30° C) [see USP for Controlled Room Temperature].

Inactive ingredients

Bubblegum flavor, citric acid, FD&C Red #40, methylparaben, potassium citrate, propylene glycol, propylparaben, purified water, sorbitol, sucralose

Questions or Comments?

Call 352.754.8587

PRINCIPAL DISPLAY PANEL - 473 mL Bottle Label

NDC 58605-306-16

Maxi-Tuss PE

Antihistamine • Nasal Decongestant

Sugar Free • Alcohol Free
• Gluten Free

Each teaspoonful (5 mL)
for oral administration contains:
Brompheniramine Maleate 2 mg
Phenylephrine HCl 5 mg

Bubblegum Flavor

Tamper evident by foil seal under cap.
Do not use if foil seal is broken or
missing.

Manufactured for:
MCR American Pharmaceuticals, Inc.
Brooksville, FL 34604

16oz. (473 mL)